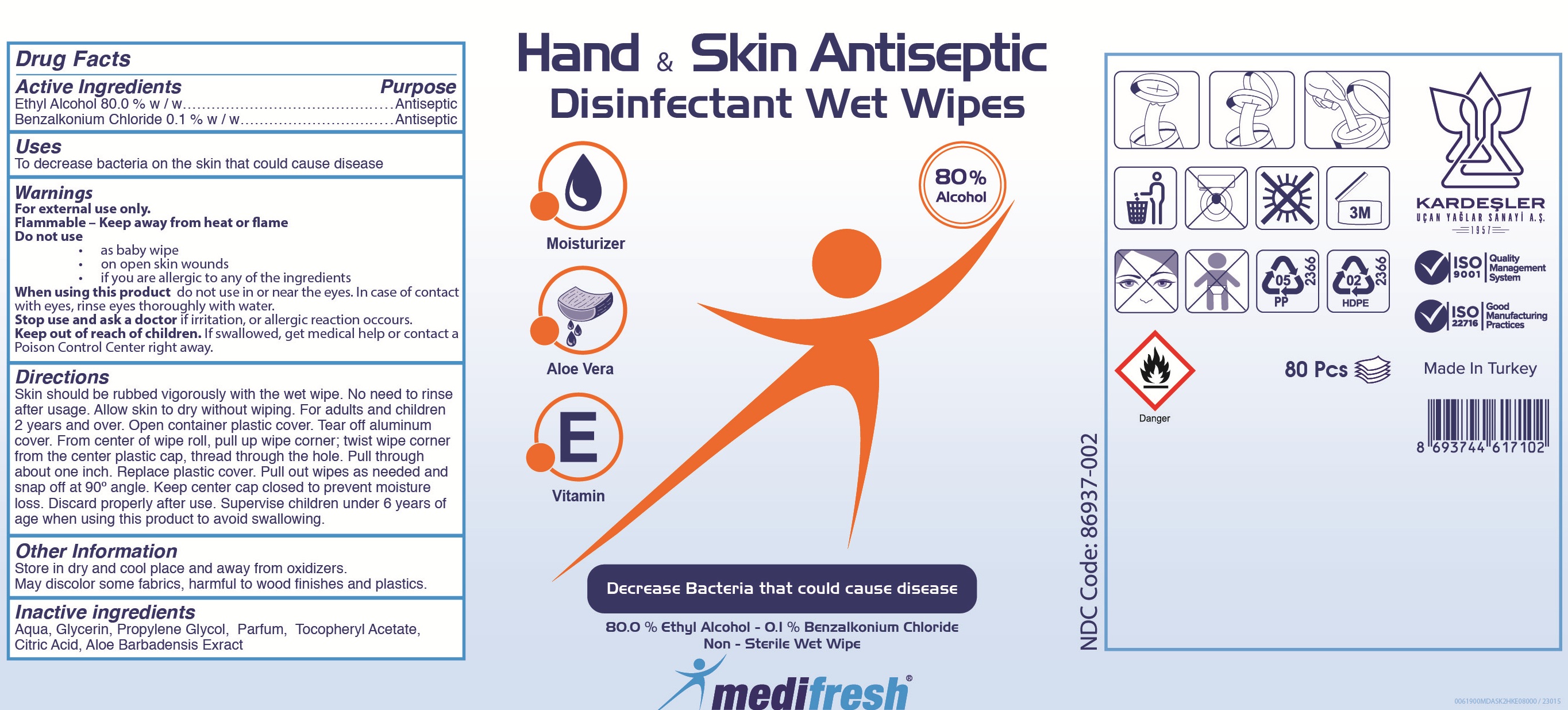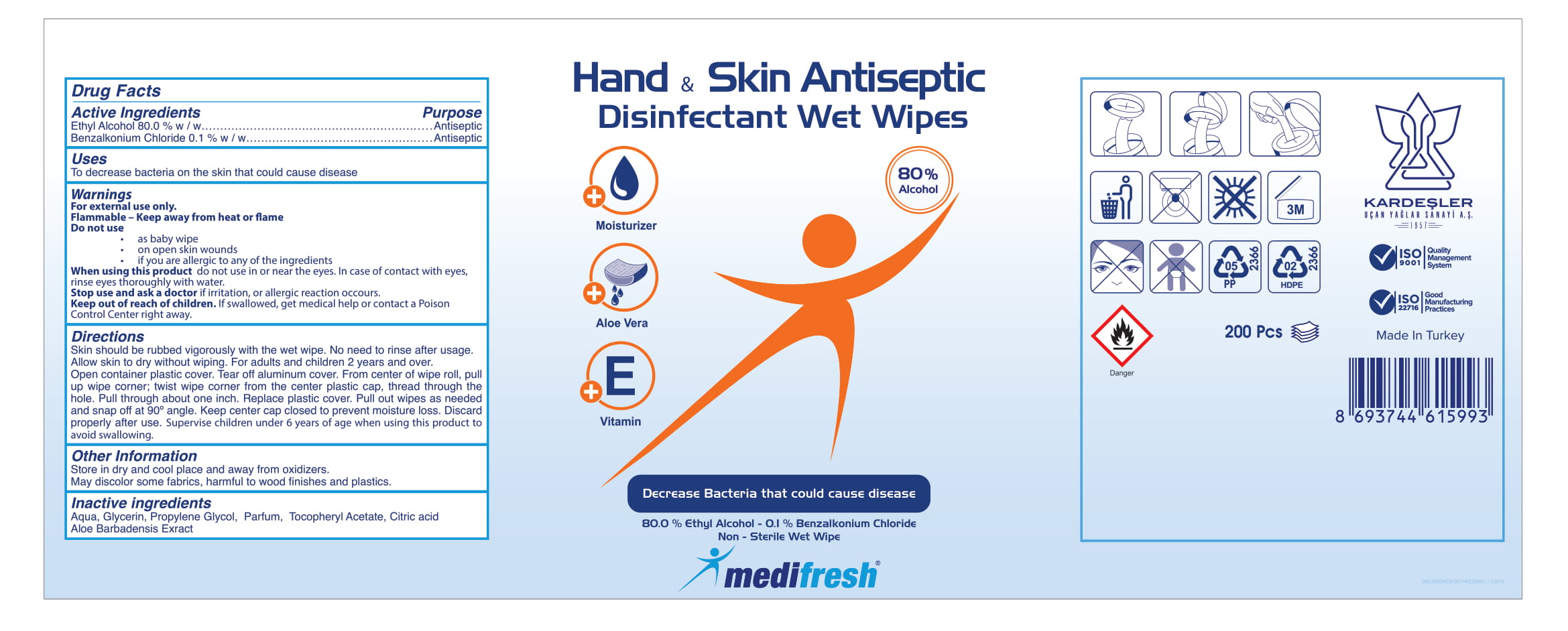 DRUG LABEL: Medifresh Hand Skin Antiseptic Disinfectant Wet Wipes
NDC: 86937-002 | Form: CLOTH
Manufacturer: KARDESLER UCAN YAGLAR SANAYI ANONIM SIRKETI
Category: otc | Type: HUMAN OTC DRUG LABEL
Date: 20200820

ACTIVE INGREDIENTS: BENZALKONIUM CHLORIDE 0.1 g/100 g; ALCOHOL 80 g/100 g
INACTIVE INGREDIENTS: ALPHA-TOCOPHEROL ACETATE 0.05 g/100 g; CITRIC ACID MONOHYDRATE 0.04 g/100 g; ALOE VERA LEAF 0.02 g/100 g; PROPYLENE GLYCOL 0.2 g/100 g; GLYCERIN 0.2 g/100 g; WATER 19.19 g/100 g

MEDIFRESH HAND&SKIN ANTISEPTIC DISINFECTANT WET WIPES

This is a hand sanitizer manufactured according to the Temporary Policy for Preparation of Certain Alcohol-Based Hand Sanitizer Products During the Public Health Emergency (CoViD-19); Guidance for Industry.

The hand sanitizer is manufactured using only the following United States Pharmacopoeia (USP) grade ingredients in the preparation of the product (percentage in final product formulation) consistent with World Health Organization (WHO) recommendations:

1. Alcohol (ethanol) (USP or Food Chemical Codex (FCC) grade) (80%, (w/w)) in an aqueous solution denatured according to Alcohol and Tobacco Tax and Trade Bureau regulations in 27 CFR part 20.
2. Benzalkonium Chloride (0.1% w/w).
3. Glycerol (0.2% w/w).
4. Tocopheryl Acetate (0.05% w/w)
5. Propylene Glycol (0.2% w/w).
6. Aloe Barbadensis Extract (0.02% w/w)
7. Citric acid (0.04% w/w)
8. Sterile distilled water or boiled cold water.

The firm does not add other active or inactive ingredients. Different or additional ingredients may impact the quality and potency of the product.

Active Ingredient(s)

Alcohol 80% w/w

Benzalkonium Chloride 0.1% w/w .

Purpose: Antiseptic

Purpose

Antiseptic, Hand & Skin Sanitizer

Use

Skin should be rubbed vigorously with the wet wipe. No need to rinse after usage. Allow skin to dry without wiping. For adults and children 2 years and over.

Warnings

For external use only. Flammable. Keep away from heat or flame

Do not use

- as baby wipe
- on open skin wounds
- if you are allergic to any other ingredient.

When using this product do not use in or near the eyes. In case of contact with eyes, rinse eyes thoroughly with water.
Keep out of reach of children. If swallowed, get medical help or contact a Poison Control Center right away.

Stop use and ask a doctor if irritation or allergic reaction occurs.

Keep out of reach of children. If swallowed, get medical help or contact a Poison Control Center right away.

Directions

- Open contaniner plastic cover. Tear off aluminum cover. From center of wipe roll, pull up wipe corner; Twist wipe corner from the center plastic cap, thread through the hole. Pull through about one inch. Replace plastic cover. Pull out wipes as needed and snap off at 90 angle. Wipe skin,hands, wrist and elbow ensuring wetting completely. Do not rinse after usage. Keep center cap closed to prevent moisture loss. Discard properly after use.
- Supervise children under 6 years of age when using this product to avoid swallowing.

Other information

- Store in dry and cool place and away from oxidizers.
- May discolor some fabrics, harmful to wood finishes and plastics.

Inactive ingredients

Aqua, Glycerol, Propylene Glycol, Parfum, Tocopheryl Acetate, Citric acid, Aloe Barbadensis Extract

Package Label - Principal Display Panel

80 PCS NDC: 86937-002-02

200 PCS NDC: 86937-002-01